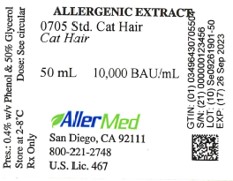 DRUG LABEL: Standardized Cat Hair
NDC: 49643-705 | Form: INJECTION
Manufacturer: Allermed Laboratories, Inc.
Category: prescription | Type: HUMAN PRESCRIPTION DRUG LABEL
Date: 20250603

ACTIVE INGREDIENTS: FELIS CATUS HAIR 10000 [BAU]/1 mL
INACTIVE INGREDIENTS: SODIUM CHLORIDE 0.0025 g/1 mL; SODIUM BICARBONATE 0.00125 g/1 mL; GLYCERIN 0.53 mL/1 mL; WATER; PHENOL 0.004 g/1 mL

Standardized Cat Hair Allergenic Extract

WARNINGS

This allergenic product is intended for use by physicians who are experienced in the administration of allergenic extracts and the emergency care of anaphylaxis, or for use under the guidance of an allergy specialist. Standardized Cat Hair Extract is not directly interchangeable with Standardized Cat Pelt Extract or Cat Extracts labeled in Allergy Units (AU/mL) The initial dose must be based on skin testing as described in the dosage and administration section of this insert. Patients being switched from other types of cat extracts to Standardized Cat Hair Extract should be started as though they were coming under treatment for the first time Patients should be instructed to recognize adverse reaction symptoms and cautioned to contact the physicians office if reaction symptoms occur. As with all allergenic extracts, severe systemic reactions may occur. In certain individuals these reactions may result in death.
Patients should be observed for at least 20 minutes following treatment and emergency measures as well as personnel trained in their use should be immediately available in the event of a life threatening reaction.

This product should not be injected intravenously (see Dosage and Administration). Refer also to the warnings, precautions, adverse reactions and overdosage sections below.

Serious adverse reactions to this product should be reported to MEDWATCH, Food and Drug Administration, 5600 Fishers Lane, MD 20852-9787. Telephone 1-800-822-7967 or www.vaers.hhs.gov.

DESCRIPTION

Standardized Cat Hair Extract is a clear, light yellow to amber solution of the allergens of cat hair, extracted in buffered saline containing sodium chloride, sodium bicarbonate and 50% glycerol by volume. Phenol at 0.4% w/v is added as a preservative. Source material for the extract is obtained from the hair of the domestic cat The importance of surface allergens in cat allergy has been shown in several investigations (1,2,3).

Standardization
The potency of Standardized Cat Hair Extract is based on the amount of Fel d1 allergen in the extract. Extract containing 5-9.9 units per mL is assigned a potency of 5,000 Bioequivalent Allergy Units (BAU/mL). Extract containing 10-19.9 Fel d1 units is assigned a potency of 10,000 BAU/mL. BAU/mL values are based on quantitative skin testing.

The primary allergen of Standardized Cat Hair Extract is Fel d1. Standardized Cat Pelt Extract contains Fel d1, as well as non-Fel d1 allergens. The latter are believed lobe
components of cat serum, such as albumin. Pelt extracts have a higher protein content than hair extracts, and the isoelectric focusing (IEF) pattern of the pelt extract reveals protein bands that are not present in cat hair extracts. The IEF pattern of cat hair extracts shows primarily Fel d1 allergen without serum components.

The importance of Fel d1 as a means of standardizing the potency of cat extract is based on the following observations:
1. The intensity of skin reactions to cat extract correlates with the Fel d1 content of the extract in most cat sensitive patients(1).
2. The absorption of cat extract with monospecific antisera to Fel d1 causes a reduction in the allergenic activity of cat extract (1).
3. The precipitin arc of Fel d1 in cat extract binds most of the IgE antibody in sera obtained from cat allergic individuals (2).

CLINICAL PHARMACOLOGY

Positive skin tests with allergenic extract are the result of histamine release from mast cells sensitized with allergen specific IgE. The exact mechanisms by which immunotherapy relieves symptoms of allergy are still under investigation. Elevations in allergen-specific IgG antibodies and an increase in the activity of T suppressor lymphocytes appear to be some of the immunologic changes that occur from hyposensitization (4, 5, 6).

INDICATIONS AND USAGE

Studies have shown that skin tests with cat extract are useful in the diagnosis of cat allergy. As a rule, persons with cat allergy have positive skin reactions when tested with cat extract, and non-allergic individuals rarely react (7, 8, 9). However, the relationship between a positive skin test and the appearance of clinical symptoms after exposure to a cat is not absolute, i.e., some skin-test positive persons do not experience allergic symptoms after exposure (10). Failure to experience symptoms may be dose related, since it is known that cats vary significantly in the amount of Fel d1 they produce (11).

The efficacy of cat extract immunotherapy in the treatment of bronchial asthma has been shown in two studies (12, 13) A reduction in bronchial sensitivity was observed in five patients with cat allergy, whereas no reduction was observed in placebo treated, cat-allergic patients.

CONTRAINDICATIONS

Standardized Cat Hair Extract should not be used for immunotherapy in persons who do not have cat related allergic symptoms and a positive skin test to the extract.

WARNINGS

Standardized Cat Hair Extract may cause local or severe life-threatening reactions when administered to highly sensitive individuals. Physicians who use this product should be familiar with the clinical use of allergenic extract and have the necessary emergency
equipment and medications available to treat systematic allergic reactions See Precautions, Adverse Reactions and Overdosage.

Standardized Cat Hair Extract should not be used interchangeably with Standardized Cat Pelt Extracts or previously standardized cat extracts labeled in Allergy Units per mL. Cat hair extracts labeled in BAU/mL made by other manufacturers should be tested for bioequivalency by serial titration skin testing before these products are used in patients who have previously received Allermed Standardized Cat Hair Extract.

The dosage of Standardized Cat Hair Extract must be reduced when starting a patient on a new lot of Standardized Cat Hair Extract containing the same amount of Fel d1 units per mL.

This is necessary due to a possible loss of potency during storage in the physician's office.

The dose of the new lot of extract should not exceed 1/4 the last dose given from the old lot of extract.

Any evidence of a strong local reaction or systemic reaction following the administration of Standardized Cat Hair Extract requires a reduction in dosage during the initial stages of immunotherapy, as well as during maintenance therapy.

PRECAUTIONS

GENERAL: Do not inject intravenously. After the needle is inserted subcutaneously, the plunger should be withdrawn slightly to check for the presence of blood in the syringe If blood is observed, a new injection should be prepared and given at another site, Observing the same precautions. The extract should be stored at 2°C-8°C. Dilutions of the 10,000 BAU/mL concentrate should be made with buffered saline containing human serum albumin for maximum stability. However, regardless of diluent type, diluted extract should be checked by skin test on a known cat-allergic individual if loss of potency is suspected.

PREGNANCY CATEGORY C: Animal reproduction studies have not been conducted with Standardized Cat Hair Extract . It is also not known whether allergenic extract can cause fetal harm when administered to a pregnant woman or can affect reproduction capacity. Standardized Cat Hair Extract should be given to a pregnant woman only if clearly needed.

PATIENT INSTRUCTIONS: Patients should be instructed to remain in the physician's office for at least 20 minutes after skin testing and after each treatment injection, and immediately notify the physician if symptoms of a generalized reaction or shock occur.

CARCINOGENESIS, MUTAGENESIS, IMPAIRMENT OF FERTILITY: Long term studies have not been conducted with Standardized Cat Hair Extract to determine their potential for carcinogenesis, mutagenesis, and impairment of fertility.

NURSING MOTHERS: Data are not available on the secretion of Standardized Cat Hair Extract in human milk and it is not known what effect this might have on the nursing infant.

PEDIATRIC USE: The dose of Standardized Cat Hair Extract recommended for children is the same as that used for adults, except in the injection of large doses of extract for treatment. In this case, the amount of extract given to a child may be modified so that the discomfort of the injection is minimized.

DRUG INTERACTION: The skin test response to Standardized Cat Hair Extract in sensitive persons may be suppressed by previous treatment with antihistamines and drugs with antihistamine activity. Treatment with beta-blocking drugs may make patients refractory to the usual dose of epinephrine, in the event epinephrine is required to control an adverse allergic reaction. Caution should be observed in the following circumstances:

EXTREME SENSITIVITY TO CATS: Determined from previous anaphylaxis following skin testing or natural exposure.

AUTOIMMUNE DISEASE: Individuals with autoimmune disease may be at risk, due to the possibility of routine immunizations exacerbating symptoms of the underlying disease.

MYOCARDIAL INFARCTION: Patients who have experienced a recent myocardial infarction may not be able to tolerate immunotherapy. As in all of the above circumstances, the benefit to risk ratio must be carefully evaluated Standardized Cat Hair Extract should be temporarily withheld from patients if any of the following conditions exist: (1) severe symptoms of rhinitis and/or asthma; (2) infection or flu accompanied by fever, and (3) exposure to excessive amounts of clinically relevant allergen prior to a scheduled injection.

ADVERSE REACTIONS

Local Reactions From Skin Testing
Large local reactions may result from skin tests with Standardized Cat Hair Extract. To help prevent this, a patient should be skin tested initially by the prick or scratch method. If a positive response is NOT observed, an intradermal skin test may be performed with a more dilute solution of the extract. Oral antihistamines and topical corticosteroids may be administered to relieve itching and swelling resulting from large skin test reactions.

Local Reactions From Subcutaneous Injections
The occurrence of a hive 5 to 15 minutes after the subcutaneous injection of extract is usually due to leakage of extract into the skin along the needle tract. Firm pressure (not rubbing) at the site of injection immediately after withdrawal of the needle will usually prevent this reaction. It does not require a reduction in dosage. However, a strong local reaction with erythema and edema which persists at the injection site for several hours indicates that too much extract has been given. Failure to note this response may result in a serious generalized reaction. Treatment should be altered as follows:

1. Additional injections should not be given until all evidence of the reaction has disappeared.
2. The next injection administered should be 50% of the last nonreacting dose or less, depending upon the size and severity of the local reaction.
3. Subsequent injections should be continued at the reduced dosage unless the physician responsible for treatment believes that it is safe to increase the dose, and that possible clinical improvement would result from the administration of a larger dose of extract.

Systemic Reactions
Systemic reactions may range from a mild exacerbation of the patient's allergic symptoms to hives, anaphylactic shock, or even death from anaphylaxis. The reaction usually occurs 5 to 20 minutes after injection. As a rule, the more quickly a reaction develops, the more serious it is likely to become. Symptoms may include sneezing, coughing, itching, shortness of breath, abdominal cramps, vomiting, diarrhea, tachycardia, hypotension and respiratory failure in severe cases. The reaction is usually stopped by the subcutaneous injection of Epinephrine HCL 1:1,000 (See Overdosage below). The oral administration of antihistamines and the placement of a tourniquet proximal to the injection site are helpful adjuncts. In the event that additional measures are required, it may be necessary to treat the patient for BRONCHOSPASM with intravenous aminophylline, intravenous fluids and corticosteroids; for HYPOTENSION with vasopressors, volume repletion, isoproterenol and corticosteroids; for LARYNGEAL OBSTRUCTION with oxygen and tracheotomy and for CARDIAC ARREST with cardiopulmonary resuscitation and other appropriate measures.

OVERDOSAGE

Severe generalized symptoms or anaphylaxis following an injection must be treated immediately with Epinephrine HCL 1:1,000 as follows: Usual Dosage-Infants under 2 years 0.05 to 0.1 cc; children under 12 years 0.1 to 0.2 cc; persons over 12 years 0.3 to 0.5 cc, repeated as necessary every 10 to 15 minutes. Placement of a tourniquet above the site of injection may be helpful in controlling the absorption of the extract. It should be released every 10 minutes and reapplied as needed. Intravenous antihistamines and hydrocortisone also may be used, but only after sufficient epinephrine has been given (See Adverse Reactions).

DOSAGE AND ADMINISTRATION

Diagnosis: Concentrated extract (10,000 BAU/mL) may be used for scratch or prick-puncture testing. Puncture tests performed with a bifurcated needle in ten cat allergic persons showed a mean wheal diameter of 6.6 mm (S.D. 1.3) with a mean sum of erythema of 57.3 mm (S.D. 10.4).
Intradermal tests with serial three-fold dilution of the 10,000 BAU/mL showed the following results:

Serial 3-Fold Dilutions of 10,000 BAU/mL Extract
Subject | 1 | 2 | 3 | 4 | 5 | 6 | 7 | 8 | 9 | 10 | 11 | 12 | 13 | 14 | 15
1 |  |  |  |  |  |  |  |  |  |  |  | X
2 |  |  |  |  |  |  |  |  |  |  |  |  |  | X
3 |  |  |  |  |  |  |  |  |  |  |  |  | X
4 |  |  |  |  |  |  |  | X
5 |  |  |  |  |  |  | X
6 |  |  |  |  |  |  | X
7 |  |  |  |  |  |  |  |  |  |  |  |  |  | X
8 |  |  |  |  |  |  |  |  |  | X
9 |  |  |  |  |  |  |  |  | X
10 |  |  |  |  |  |  |  |  |  |  | X

The mean three-fold dilution eliciting a response of 50 mm sum of erythema diameters was 11.120 (S.D. 2,38). The number of BAU/mL required to elicit this response was 0.05 (range 0.0003 to 9.24 BAU/mL). This concentration is approximately a 1:200,000 v/v dilution of the 10,000 BAU/mL extract.
Extract for intradermal testing should be used as follows:

1. Patients with a positive scratch or prick test to Standardized Cat Hair Extract. It is not advisable to perform an intradermal skin test in these patients.
2. Patients with a negative scratch or prick test to Standardized Cat Hair Extract. Patients who do not react to a scratch or prick test with the 10,000 BAU/mL concentrate maybe tested intradermally with 0.05 mL of a 1:2,000 v/v dilution of the concentrate (5 BAU/mL). If the test is negative, a second test should be performed with 0.05 mL of a 1:200 v/v dilution of concentrate (50 BAU/mL).
3. Patients tested only by the intradermal method with Standardized Cat Hair Extract. Patients suspected of being highly allergic to cats should be tested with 0.05 mL of a 1:200,000 v/v dilution (0.05 BAU/mL) of the concentrate. A negative test should be followed by repeat tests using 10 fold stronger concentrations until the maximum dose of 0.05 mL of a 1:200 v/v dilution (50 BAU/mL) is reached.

Interpretation Of Skin Tests:

The interpretation of skin tests should be based on the size of the erythema and wheal response to the allergen compared to a negative saline control. A suggested method of scoring skin tests is shown below. Measurements refer to the longest (single), diameter of erythema and wheal response.

Scratch and Prick Test
A negative test shows only a slight red area at the site of scarification or prick penetration. Positive tests are scored as follows:
1 + Erythema with a 5 mm wheal
2 + Erythema with a 5 -10 mm wheal
3 + Erythema with a 10 - 15 mm wheal
4 + Erythema with a wheal 15 mm (or larger) with pseudopodia

Intradermal Test
A negative test shows no change in the appearance and size of the 5mm wheal created by the 1.D. injection of 0.05 mL of extract. Positive tests are scored as follows:
1 + Erythema 10 - 20 mm with a 5 -10 mm wheal
2 + Erythema 20 - 30 mm with a 5 -10 mm wheal
3 + Erythema 30 - 40 mm with a 10 - 15 mm wheal
4 + Erythema greater than 40 mm with a 15 mm wheal (or larger) with pseudopodia

Immunotherapy

Allergenic extract should be administered subcutaneously in the outer aspect of the upper arm using a sterile tuberculin syringe and needle. The skin should be cleaned with 70% alcohol and aseptic technique should be observed in removing the extract from the vial. Care must be taken to avoid injecting the extract into a blood vessel because of the potential hazard of anaphylaxis.

Standardized Cat Hair Extract must be diluted before administration to new patients. As a precaution against overdose, a skin test with the intended starting dose should be done to help evaluate the patient's sensitivity to the product. If the skin response is larger than 5/15 mm (edema/erythema), the extract should be diluted before it is given subcutaneously. The doses shown in the Dosage Schedule may be followed unless the patient's skin test response and allergic history indicate that more dilute extract should be used.

Little is known about the required accumulated dosage of Fel d1 (and other allergens that may be present in cat extract) that is needed to relieve symptoms. However, studies with other allergenic substances have shown that high dose immunotherapy is most efficacious in the treatment of allergic rhinitis and asthma. The amount of cat extract that is tolerated during immunotherapy depends upon the sensitivity of the patient. In one study in which patients with cat asthma were treated for a period of one year, the accumulated dose of Fel d1 varied from 3.6 to 115.8 (median 46.2) units (13). A burning sensation immediately following the injection of extract from the concentrate is due to the glycerol in the extract. It should not be interpreted as an adverse allergic response.

Patients who have received allergenic extract for maintenance therapy SHOULD NOT be given the same dose from a fresh vial of extract. IT IS ADVISABLE TO REDUCE THE DOSAGE OF FRESH EXTRACT TO ONE-FOURTH THE AMOUNT GIVEN FROM A PREVIOUS LOT.

Dosage Schedule for Standardized Cat Hair Extract (The safety and efficacy of this schedule has not been determined by well-controlled clinical trials.) [BAU = Bioequivalent Allergy Units per mL]
 | Vial #1; 0.05 BAU | Vial #2; 0.5 BAU | Vial #3; 5 BAU | Vial #4; 50 BAU | Vial #5; 500 BAU | Vial #6; 5,000 BAU
 |  |  | frequency twice weekly
No. | mL | mL | mL | mL | mL | mL
1 | 0.05 | 0.05 | 0.05 | 0.05 | 0.05 | 0.05
2 | 0.1 | 0.1 | 0.1 | 0.1 | 0.1 | 0.1
3 | 0.2 | 0.2 | 0.2 | 0.2 | 0.2 | 0.2
4 | 0.3 | 0.3 | 0.3 | 0.3 | 0.3 | 0.3
5 | 0.4 | 0.4 | 0.4 | 0.4 | 0.4 | 0.4

v/v dilutions of concentrate containing 10,000 BAU per mL required to make the above concentrations.
BAU per mL | v/v Dilution of Concentrate
0.05 | 1:200,000
0.5 | 1:20,000
5.0 | 1:2,000
50.0 | 1:200
500.0 | 1:20
5,000.0 | 1:2

HOW SUPPLIED

Standardized Cat Hair Extract containing 10,000 BAU per mL is supplied in 5 mL dropper vials for scratch or prick testing and in 10 mL, 30 mL and 50 mL vials as concentrate.

STORAGE AND HANDLING

Extract should be stored at 2°C to 8°C since higher temperatures may adversely affect stability. Do not freeze.

REFERENCES

1. Ohman, J.L. Studies of the origin and environmental occurrence of cat allergen. J. Allergy Clin. Immunol., 69:127, 1982.
2. Anderson, M.G., and Baer, H.. Allergenically active components of cat allergen extracts. J. Immunol., 127:972, 1981.
3. Spain, W.C., Gillson, R.E. and Strauss, M.B.. Comparative immunologic studies with salivary and epithelial extracts of the dog, cat and rabbit. J. Allergy., 13:563, 1942.
4. Levy, D.A., Lichtenstein, L.M., Goldstein E.O. and Ishizaka, K.. Immunologic and cellular changes accompanying the therapy of pollen allergy. J. Clinical Investigations. 50:360, 1971.
5. Evans, R., Pence, H., Kaplan, H and Rocklin, R. The effect of immunotherapy on humoral and cellular response in ragweed hayfever, J. Clinical Investigations. 57:1378, 1976.
6. lshizaka, K. Cellular events in the IgE antibody response. Adv. in Immunology. 23:50, 1976.
7. Muljono. I.S. and Voorhost, R. Atopy to dander from domestic animals, Allergie Immunol. 24:50, 1978.
8. Curran, W. andGoldman, G. The incidence of immediately reacting allergy skin tests in a normal adult population. Ann. Internal Med. 55:777, 1961.
9. Fontana, V.J.,Whittig, H. and Holt Jr., L.E. Observations on the specificity of the skin test. The incidence of positive skin tests in allergic and non-allergic children. J. Allergy. 34:348, 1963.
10. Sarsfield, J.K., Boyle, A.G. Rowell, E.M. and Moriarty, S.C.. Pet sensitivities in asthmatic children. Arch. Dis., Childhood. 51:186, 1976.
11. Ohman, J.L., Baer, H., Anderson, M.C. Leitermann, K. and Brown, P. Surface washes of living cats: An improved method of obtaining clinically relevant allergen. J. Allergy Clin. Immunol. 72:288, 1983.
12. Taylor, W.W. Ohman, J.L. and Lowell, F.C. Immunotherapy in cat-induced asthma. Double-blind trial with evaluation of bronchial response to cat allergen and histamine. J.
Allergy Clin. lmmunol. 61:283, 1978.
13. Van Metre, T.E., Marsh, D.G., Adkinson Jr., N.F., Kagey-Sobotka, A., Khattignavong, A., Norman Jr., P.S. and Rosenberg, G.L. Immunotherapy for cat asthma. J. Allergy Clin. Immunol., 82:1055, 1988.